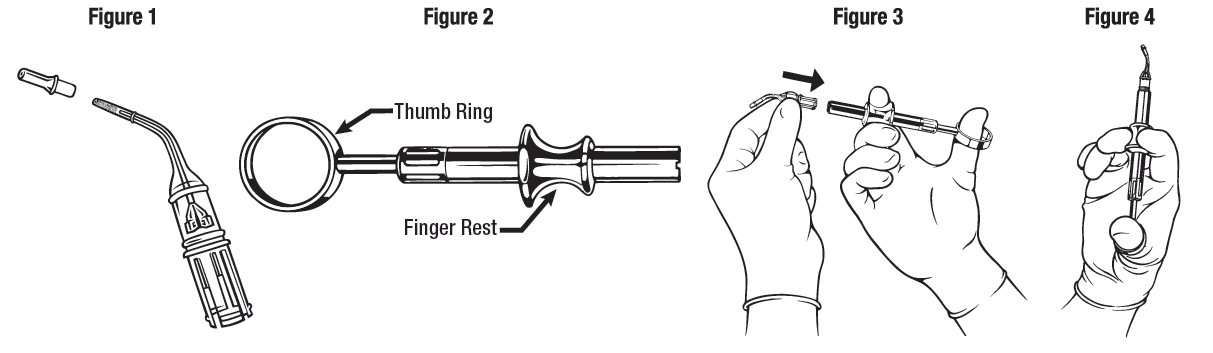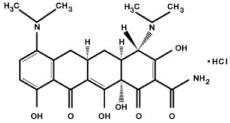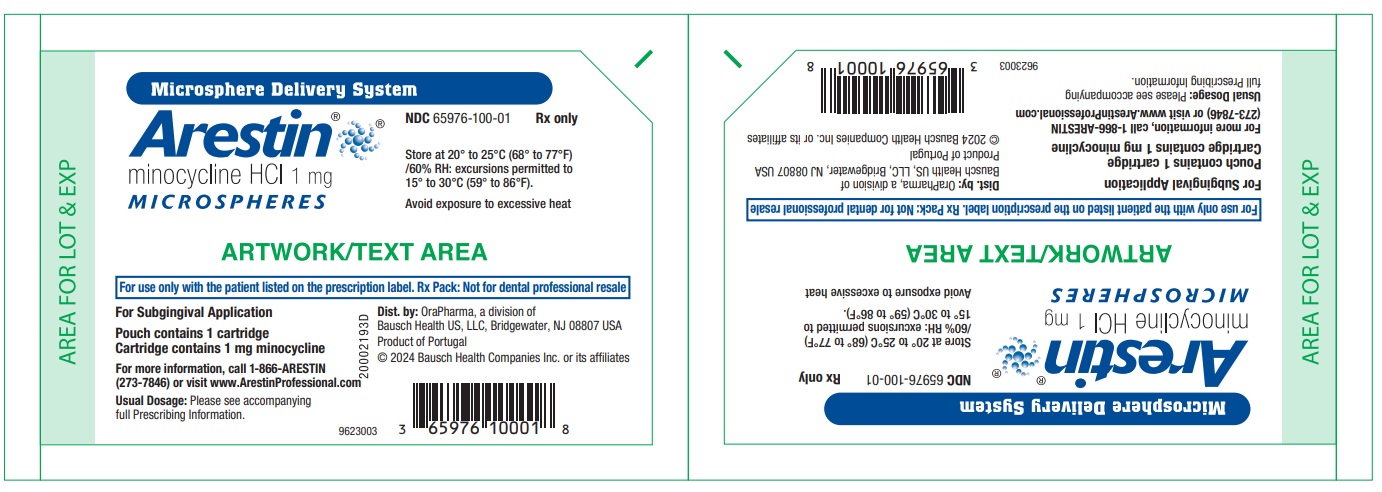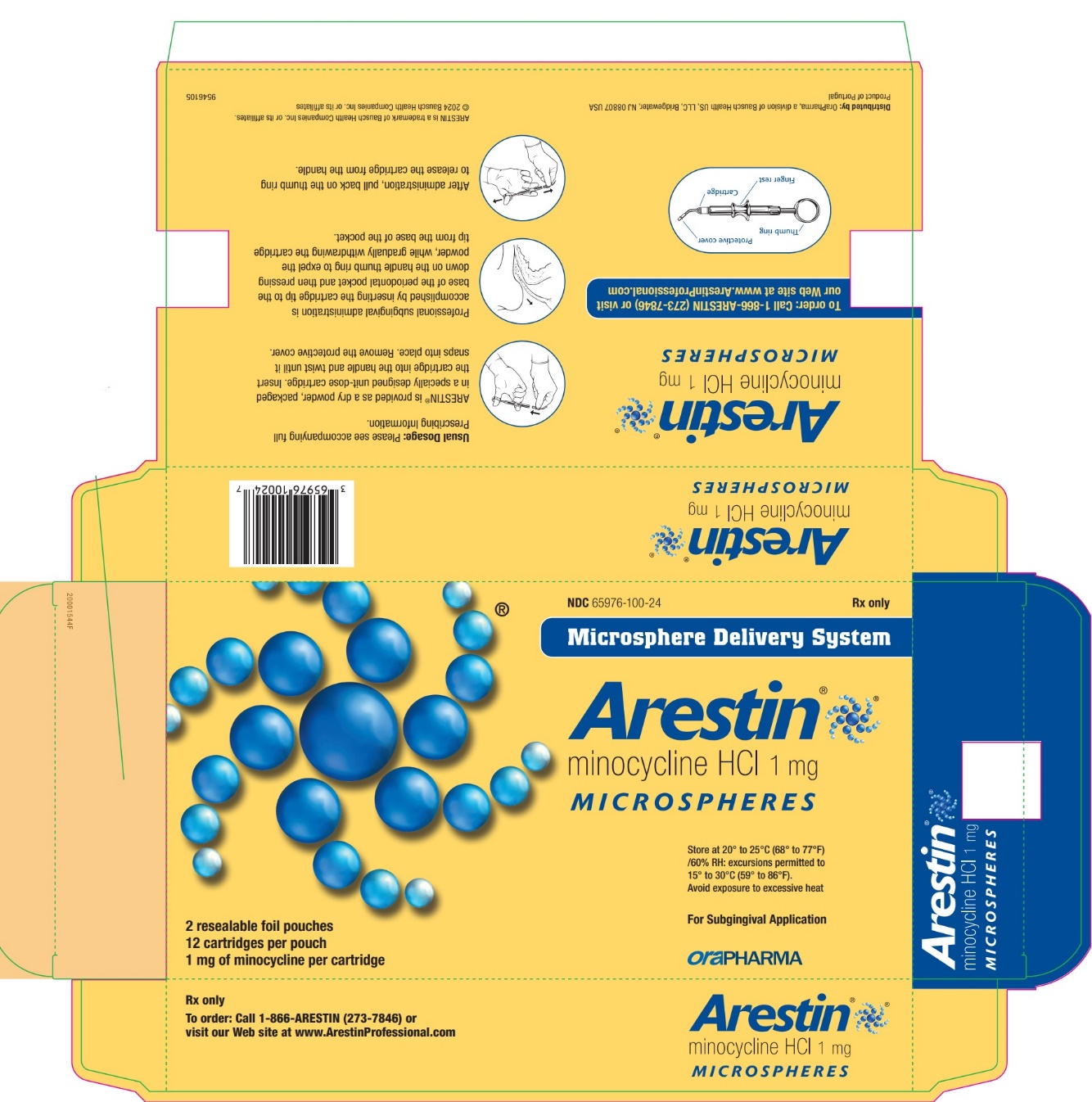 DRUG LABEL: Arestin
NDC: 65976-100 | Form: POWDER
Manufacturer: OraPharma, Inc.
Category: prescription | Type: HUMAN PRESCRIPTION DRUG LABEL
Date: 20240531

ACTIVE INGREDIENTS: Minocycline Hydrochloride 1 mg/1 1

ARESTIN®
(minocycline hydrochloride) microspheres, 1 mg

DESCRIPTION

ARESTIN (minocycline hydrochloride) microspheres, 1 mg is a subgingival sustained-release product containing the antibiotic minocycline hydrochloride incorporated into a bioresorbable polymer, Poly (glycolide-co-dl-lactide) or PGLA, for professional subgingival administration into periodontal pockets. Each unit-dose cartridge delivers minocycline hydrochloride equivalent to 1 mg of minocycline free base.

The molecular formula of minocycline hydrochloride is C23H27N3O7 ● HCl, and the molecular weight is 493.94. The structural formula of minocycline hydrochloride is:

CLINICAL PHARMACOLOGY

Mechanism of Action

The mechanism of action of ARESTIN as an adjunct to scaling and root planing procedures for reduction of pocket depth in patients with adult periodontitis is unknown.

Microbiology

Minocycline, a member of the tetracycline class of antibiotics, has a broad spectrum of activity. It is bacteriostatic and exerts its antimicrobial activity by inhibiting protein synthesis. In vitro susceptibility testing has shown that the organisms Porphyromonas gingivalis, Prevotella intermedia, Fusobacterium nucleatum, Eikenella corrodens, and Actinobacillus actinomycetemcomitans, which are associated with periodontal disease, are susceptible to minocycline at concentrations of ≤8 mcg/mL; qualitative and quantitative changes in plaque microorganisms have not been demonstrated in subjects with periodontitis, using this product.

The emergence of minocycline-resistant bacteria in single-site plaque samples was studied in subjects before and after treatment with ARESTIN at 2 centers. There was a slight increase in the numbers of minocycline-resistant bacteria at the end of the 9-month study period; however, the number of subjects studied was small and the clinical significance of these findings is unknown.

The emergence of minocycline-resistant bacteria and changes in the presence of Candida albicans and Staphylococcus aureus in the gastrointestinal tract were studied in subjects treated with ARESTIN in one phase 3 study. No changes in the presence of minocycline-resistant bacteria or Candida albicans or Staphylococcus aureus were seen at the end of the 56-day study period.

Pharmacokinetics

In a pharmacokinetic study, 18 subjects (10 men and 8 women) with moderate to advanced chronic periodontitis were treated with a mean dose of 46.2 mg (25 to 112 unit doses) of ARESTIN. After fasting for at least 10 hours, subjects received subgingival application of ARESTIN (1 mg per treatment site) following scaling and root planing at a minimum of 30 sites on at least 8 teeth. Investigational drug was administered to all eligible sites ≥5 mm in probing depth. Mean dose normalized saliva AUC and Cmax were found to be approximately 125 and 1000 times higher than those of serum parameters, respectively.

Clinical Studies

In 2 well-controlled, multicenter, investigator-blind, vehicle-controlled, parallel-design studies (3 arms), 748 subjects (study OPI-103A=368, study OPI-103B=380) with generalized moderate to advanced adult periodontitis characterized by a mean probing depth of 5.90 and 5.81 mm, respectively, were enrolled. Subjects received 1 of 3 treatments: (1) scaling and root planing (SRP), (2) SRP + vehicle (bioresorbable polymer, PGLA), and (3) SRP + ARESTIN. To qualify for the study, subjects were required to have 4 teeth with periodontal pockets of 6 to 9 mm that bled on probing. However, treatment was administered to all sites with mean probing depths of 5 mm or greater. Subjects studied were in good general health. Subjects with poor glycemic control or active infectious diseases were excluded from the studies. Retreatment occurred at 3 and 6 months after initial treatment, and any new site with pocket depth ≥5 mm also received treatment. Subjects treated with ARESTIN were found to have statistically significantly reduced probing pocket depth compared with those treated with SRP alone or SRP + vehicle at 9 months after initial treatment, as shown in Table 1.

Table 1: Probing Pocket Depth at Baseline and Change in Pocket Depth at 9 Months from 2 Multicenter US Clinical Trials
Time | Study OPI-103A N=368 |  |  | Study OPI-103B N=380
 | SRP Alone n=124 | SRP + Vehicle n=123 | SRP + ARESTIN n=121 | SRP Alone n=126 | SRP + Vehicle n=126 | SRP + ARESTIN n=128
PD (mm) at Baseline [Mean ± SE] | 5.88 | 5.91 | 5.88 | 5.79 | 5.82 | 5.81
PD (mm) at Baseline [Mean ± SE] | ±0.04 | ±0.04 | ±0.04 | ±0.03 | ±0.04 | ±0.04
PD (mm) Change from Baseline at 9 Months [Mean ± SE] | -1.04 | -0.90 | -1.20*†† | -1.32 | -1.30 | -1.63**††
PD (mm) Change from Baseline at 9 Months [Mean ± SE] | ±0.07 | ±0.54 | ±0.07 | ±0.07 | ±0.07 | ±0.07
SE = standard error; SRP = scaling and root planing; PD = pocket depth
Significantly different from SRP: *(P ≤0.05); **(P ≤0.001)
Significantly different from SRP + vehicle: ††(P ≤0.001)

In these 2 studies, an average of 29.5 (5-114), 31.7 (4-137), and 31 (5-108) sites were treated at baseline in the SRP alone, SRP + vehicle, and SRP + ARESTIN groups, respectively. When these studies are combined, the mean pocket depth change at 9 months was -1.18 mm, -1.10 mm, and -1.42 mm for SRP alone, SRP + vehicle, and SRP + ARESTIN, respectively.

Table 2: Numbers (Percentage) of Pockets Showing a Change of Pocket Depth ≥2 mm at

9 Months from 2 Multicenter US Clinical Trials
 | Study OPI-103A |  |  | Study OPI-103B
 | SRP Alone | SRP + Vehicle | SRP + ARESTIN | SRP Alone | SRP + Vehicle | SRP + ARESTIN
Pockets | 1046 | 927 | 1326 | 1692 | 1710 | 2082
≥2 mm (% of Total) | (31.1%) | (25.7%) | (36.5%) | (42.2%) | (40.0%) | (51.0%)
Pockets | 417 | 315 | 548 | 553 | 524 | 704
≥3 mm (% of Total) | (12.4%) | (8.7%) | (15.1%) | (13.8%) | (12.3%) | (17.3%)

SRP + ARESTIN resulted in a greater percentage of pockets showing a change of PD ≥2 mm and ≥3 mm compared to SRP alone at 9 months, as shown in Table 2.

Table 3: Mean Pocket Depth Changes (SE) in Subpopulations, Studies 103A and 103B Combined
 | SRP Alone | SRP + Vehicle | SRP + ARESTIN
Smokers | n=91; -0.96 (±0.09) mm | n=90; -0.98 (±0.07) mm | n=90; -1.24 (±0.09) mm**
Nonsmokers | n=159; -1.31 (±0.06) mm | n=159; -1.17 (±0.07) mm | n=159; -1.53 (±0.06) mm**
Subjects >50 YOA | n=21; -1.07 (±0.09) mm | n=81; -0.92 (±0.08) mm | n=107; -1.42 (±0.08) mm**
Subjects ≤50 YOA | n=167; -1.24 (±0.06) mm | n=168; -1.19 (±0.06) mm | n=142; -1.43 (±0.07) mm*
Subjects with CV Disease | n=36; -0.99 (±0.13) mm | n=29; -1.06 (±0.14) mm | n=36; -1.56 (±0.14) mm**
Subjects without CV Disease | n=214; -1.22 (±0.06) mm | n=220; -1.11 (±0.05) mm | n=213; -1.40 (±0.06) mm**
SRP = scaling and root planing; YOA = years of age; CV = cardiovascular

*SRP vs SRP + ARESTIN P ≤0.05; **SRP vs SRP + ARESTIN P ≤ 0.001

In both studies, the following patient subgroups were prospectively analyzed: smokers, subjects over and under 50 years of age, and subjects with a previous history of cardiovascular disease. The results of the combined studies are presented in Table 3.

In smokers, the mean reduction in pocket depth at 9 months was less in all treatment groups than in nonsmokers, but the reduction in mean pocket depth at 9 months with SRP + ARESTIN was significantly greater than with SRP + vehicle or SRP alone.

Table 4: Mean Pocket Depth Change in Subjects with Mean Baseline

PD ≥5 mm, ≥6 mm, and ≥7 mm at 9 Months from 2 Multicenter US Clinical Trials
Study OPI-103A |  |  |  | Study OPI-103B
Mean Baseline Pocket Depth | SRP Alone | SRP + Vehicle | SRP + ARESTIN | SRP Alone | SRP + Vehicle | SRP + ARESTIN
≥5 mm (n) | -1.04 mm; (124) | -0.90 mm; (123) | -1.20 mm*; (121) | -1.32 mm; (126) | -1.30 mm; (126) | -1.63 mm*; (128)
≥6 mm (n) | -0.91 mm; (34) | -0.77 mm; (46) | -1.40 mm*; (45) | -1.33 mm; (37) | -1.46 mm; (40) | -1.69 mm*; (25)
≥7 mm (n) | -1.10 mm; (4) | -0.46 mm; (5) | -1.91 mm; (3) | -1.72 mm; (3) | -1.11 mm; (3) | -2.84 mm; (2)

*Statistically significant comparison between SRP + ARESTIN and SRP alone

The combined data from these 2 studies also show that for pockets 5 mm to 7 mm at baseline, greater reductions in pocket depth occurred in pockets that were deeper at baseline.

INDICATIONS AND USE

ARESTIN is indicated as an adjunct to scaling and root planing procedures for reduction of pocket depth in patients with adult periodontitis. ARESTIN may be used as part of a periodontal maintenance program which includes good oral hygiene and scaling and root planing.

CONTRAINDICATIONS

ARESTIN should not be used in any patient who has a known sensitivity to minocycline or tetracyclines.

WARNINGS

THE USE OF DRUGS OF THE TETRACYCLINE CLASS DURING TOOTH DEVELOPMENT (LAST HALF OF PREGNANCY, INFANCY, AND CHILDHOOD TO THE AGE OF 8 YEARS) MAY CAUSE PERMANENT DISCOLORATION OF THE TEETH (YELLOW-GRAY BROWN). This adverse reaction is more common during long-term use of the drugs, but has been observed following repeated short-term courses. Enamel hypoplasia has also been reported. TETRACYCLINE DRUGS, THEREFORE, SHOULD NOT BE USED IN THIS AGE GROUP, OR IN PREGNANT OR NURSING WOMEN, UNLESS THE POTENTIAL BENEFITS ARE CONSIDERED TO OUTWEIGH THE POTENTIAL RISKS. Results of animal studies indicate that tetracyclines cross the placenta, are found in fetal tissues, and can have toxic effects on the developing fetus (often related to retardation of skeletal development). Evidence of embryotoxicity has also been noted in animals treated early in pregnancy. If any tetracyclines are used during pregnancy, or if the patient becomes pregnant while taking this drug, the patient should be apprised of the potential hazard to the fetus. Photosensitivity manifested by an exaggerated sunburn reaction has been observed in some individuals taking tetracyclines. Patients apt to be exposed to direct sunlight or ultraviolet light should be advised that this reaction can occur with tetracycline drugs, and treatment should be discontinued at the first evidence of skin erythema.

PRECAUTIONS

Hypersensitivity Reactions and Hypersensitivity Syndrome

The following adverse events have been reported with minocycline products when taken orally. Hypersensitivity reactions and hypersensitivity syndrome that included, but were not limited to anaphylaxis, anaphylactoid reaction, angioneurotic edema, urticaria, rash, eosinophilia, and one or more of the following: hepatitis, pneumonitis, nephritis, myocarditis, and pericarditis may be present. Swelling of the face, pruritus, fever and lymphadenopathy have been reported with the use of ARESTIN. Some of these reactions were serious. Post-marketing cases of anaphylaxis and serious skin reactions such as Stevens-Johnson syndrome and erythema multiforme have been reported with oral minocycline.

Autoimmune Syndromes

Tetracyclines, including oral minocycline, have been associated with the development of autoimmune syndromes including a lupus-like syndrome manifested by arthralgia, myalgia, rash, and swelling. Sporadic cases of serum sickness-like reaction have presented shortly after oral minocycline use, manifested by fever, rash, arthralgia, lymphadenopathy and malaise. In symptomatic patients, liver function tests, ANA, CBC, and other appropriate tests should be performed to evaluate the patients. No further treatment with ARESTIN should be administered to the patient.

The use of ARESTIN in an acutely abscessed periodontal pocket has not been studied and is not recommended.

While no overgrowth by opportunistic microorganisms, such as yeast, was noted during clinical studies, as with other antimicrobials, the use of ARESTIN may result in overgrowth of non-susceptible microorganisms including fungi. The effects of treatment for greater than 6 months have not been studied.

ARESTIN should be used with caution in patients having a history of predisposition to oral candidiasis. The safety and effectiveness of ARESTIN have not been established for the treatment of periodontitis in patients with coexistent oral candidiasis.

ARESTIN has not been clinically tested in immunocompromised patients (such as those immunocompromised by diabetes, chemotherapy, radiation therapy, or infection with HIV).

If superinfection is suspected, appropriate measures should be taken.

ARESTIN has not been clinically tested in pregnant women.

ARESTIN has not been clinically tested for use in the regeneration of alveolar bone, either in preparation for or in conjunction with the placement of endosseous (dental) implants or in the treatment of failing implants.

Information for Patients

After treatment, patients should avoid chewing hard, crunchy, or sticky foods (i.e., carrots, taffy, and gum) with the treated teeth for 1 week, as well as avoid touching treated areas. Patients should also postpone the use of interproximal cleaning devices around the treated sites for 10 days after administration of ARESTIN. Patients should be advised that although some mild to moderate sensitivity is expected during the first week after SRP and administration of ARESTIN, they should notify the dentist promptly if pain, swelling, or other problems occur. Patients should be notified to inform the dentist if itching, swelling, rash, papules, reddening, difficulty breathing, or other signs and symptoms of possible hypersensitivity occur.

Carcinogenicity, Mutagenicity, Impairment of Fertility

Dietary administration of minocycline in long-term tumorigenicity studies in rats resulted in evidence of thyroid tumor production. Minocycline has also been found to produce thyroid hyperplasia in rats and dogs. In addition, there has been evidence of oncogenic activity in rats in studies with a related antibiotic, oxytetracycline (i.e., adrenal and pituitary tumors). Minocycline demonstrated no potential to cause genetic toxicity in a battery of assays which included a bacterial reverse mutation assay (Ames test), an in vitro mammalian cell gene mutation test (L5178Y/TK+/- mouse lymphoma assay), an in vitro mammalian chromosome aberration test, and an in vivo micronucleus assay conducted in ICR mice.

Fertility and general reproduction studies have provided evidence that minocycline impairs fertility in male rats.

Pregnancy

Teratogenic Effects: (see WARNINGS).

Labor and Delivery

The effects of tetracyclines on labor and delivery are unknown.

Nursing Mothers

Tetracyclines are excreted in human milk. Because of the potential for serious adverse reactions in nursing infants from the tetracyclines, a decision should be made whether to discontinue nursing or discontinue the drug, taking into account the importance of the drug to the mother (see WARNINGS).

Pediatric Use

Since adult periodontitis does not affect children, the safety and effectiveness of ARESTIN in pediatric patients cannot be established.

ADVERSE REACTIONS

The most frequently reported non-dental, treatment-emergent adverse events in the 3 multicenter US trials were headache, infection, flu syndrome, and pain.

Table 5: Adverse Events (AEs) Reported in ≥3% of the Combined Clinical Trial Population of 3 Multicenter US Trials by Treatment Group
 | SRP Alone N=250 | SRP + Vehicle N=249 | SRP + ARESTIN® N=423
Number (%) of Subjects Treatment-emergent AEs | 62.4% | 71.9% | 68.1%
Total Number of AEs | 543 | 589 | 987
Periodontitis | 25.6% | 28.1% | 16.3%
Tooth Disorder | 12.0% | 13.7% | 12.3%
Tooth Caries | 9.2% | 11.2% | 9.9%
Dental Pain | 8.8% | 8.8% | 9.9%
Gingivitis | 7.2% | 8.8% | 9.2%
Headache | 7.2% | 11.6% | 9.0%
Infection | 8.0% | 9.6% | 7.6%
Stomatitis | 8.4% | 6.8% | 6.4%
Mouth Ulceration | 1.6% | 3.2% | 5.0%
Flu Syndrome | 3.2% | 6.4% | 5.0%
Pharyngitis | 3.2% | 1.6% | 4.3%
Pain | 4.0% | 1.2% | 4.3%
Dyspepsia | 2.0% | 0 | 4.0%
Infection Dental | 4.0% | 3.6% | 3.8%
Mucous Membrane Disorder | 2.4% | 0.8% | 3.3%

The change in clinical attachment levels was similar across all study arms, suggesting that neither the vehicle nor ARESTIN compromise clinical attachment.

Postmarketing Experience

The following adverse reaction has been identified during postapproval use of minocycline products when taken orally. Because this reaction is reported voluntarily from a population of uncertain size, it is not always possible to reliably estimate their frequency or establish a causal relationship to drug exposure.

Skin and subcutaneous tissue disorders: Acute febrile neutrophilic dermatosis (Sweet’s syndrome).

To report SUSPECTED ADVERSE REACTIONS, contact OraPharma at 1-800-321-4576 or FDA at 1-800-FDA-1088 or www.fda.gov/medwatch.

DOSAGE AND ADMINISTRATION

ARESTIN is provided as a dry powder, packaged in a unit-dose cartridge with a deformable tip (see Figure 1), which is inserted into a spring-loaded cartridge handle mechanism (see Figure 2) to administer the product.

The oral health care professional removes the disposable cartridge from its pouch and connects the cartridge to the handle mechanism (see Figures 3-4). ARESTIN is a variable dose product, dependent on the size, shape, and number of pockets being treated. In US clinical trials, up to 122 unit-dose cartridges were used in a single visit and up to 3 treatments, at 3-month intervals, were administered in pockets with pocket depth of 5 mm or greater.

The administration of ARESTIN does not require local anesthesia. Professional subgingival administration is accomplished by inserting the unit-dose cartridge to the base of the periodontal pocket and then pressing the thumb ring in the handle mechanism to expel the powder while gradually withdrawing the tip from the base of the pocket. The handle mechanism should be sterilized between patients. ARESTIN does not have to be removed, as it is bioresorbable, nor is an adhesive or dressing required.

HOW SUPPLIED

ARESTIN® (minocycline hydrochloride) microspheres, 1 mg is supplied as follows:

NDC 65976-100-01 1 unit-dose cartridge with desiccant in a heat-sealed, foil-laminated pouch

NDC 65976-100-24 12 unit-dose cartridges in 1 tray with desiccant in a heat-sealed, foil-laminated, resealable pouch. There are 2 pouches in each box.

Each unit-dose cartridge contains the product identifier “OP-1.”

Storage Conditions

Store at 20° to 25°C (68° to 77°F)/60% RH: excursions permitted to 15° to 30°C (59° to 86°F). Avoid exposure to excessive heat.

Distributed by:

OraPharma, a division of Bausch Health US, LLC
Bridgewater, NJ 08807 USA

ARESTIN is a trademark of Bausch Health Companies Inc. or its affiliates.

© 2024 Bausch Health Companies Inc. or its affiliates

Rev. 05/2024

9546405

PRINCIPAL DISPLAY PANEL - 1 mg Carton

NDC 65976-100-24

Microsphere Delivery System
Arestin®
minocycline HCl 1mg
MICROSPHERES

Store at 20° to 25°C (68° to 77°F)
/60% RH: excursions permitted to
15° to 30°C (59° to 86°F).

Avoid exposure to excessive heat

For Subgingival Application

Rx only

To order: Call 1-866-ARESTIN (273-7846)
or visit our Web site at www.ArestinProfessional.com

oraPHARMA

2 resealable foil pouches
12 cartridges per pouch
1 mg of minocycline

Principal Display Panel – 1 mg pouch containing 1 cartridge

Microsphere Delivery System
Arestin®
minocycline HCl 1 mg
MICROSPHERES

For use only with the patient listed on the prescription label. Rx Pack: Not for dental professional resale
For Subgingival Application
Rx only
Pouch contains 1 cartridge
Cartridge contains 1 mg minocycline

For more information, call 1-866-ARESTIN
(273-7846) or visit www.ArestinProfessional.com

Distributed by:

OraPharma, a division of
Bausch Health US, LLC
Bridgewater, NJ 08807 USA

© 2020 Bausch Health Companies Inc. or its affiliates

Usual Dosage: Please see accompanying
full Prescribing Information.